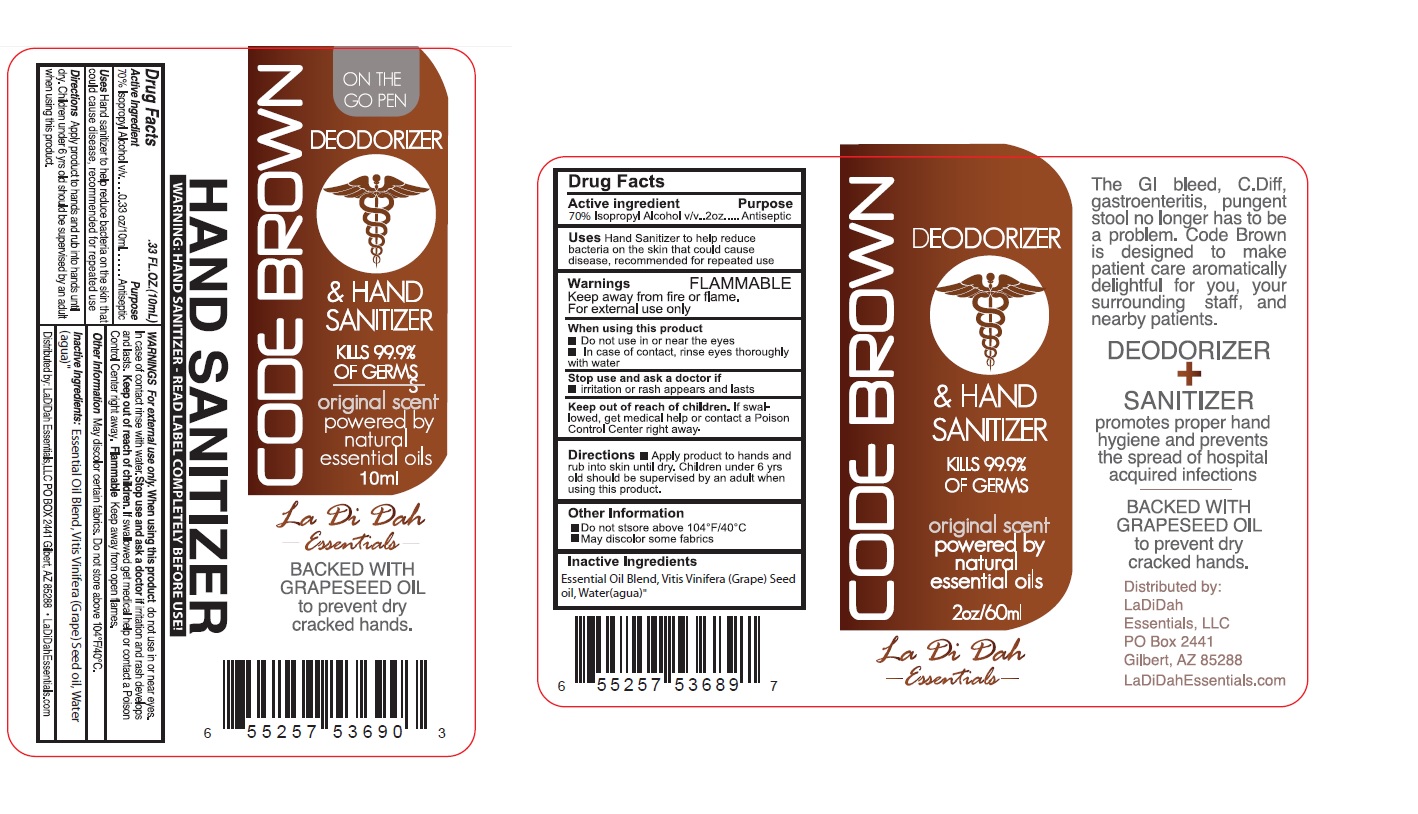 DRUG LABEL: CODE BROWN
NDC: 70913-001 | Form: LIQUID
Manufacturer: Ladidah Essentials, Llc
Category: otc | Type: HUMAN OTC DRUG LABEL
Date: 20160817

ACTIVE INGREDIENTS: ISOPROPYL ALCOHOL 70 mL/100 mL
INACTIVE INGREDIENTS: GRAPE SEED OIL; WATER

CODE BROWN DEODORIZER & HAND SANITIZER

Active Ingredient

70% Isopropyl Alcohol v/v

Purpose

Antiseptic

INDICATIONS AND USAGE

Uses Hand sanitizer to help reduce bacteria on the skin that could cause disease, recommended for repeated use.

Warnings FLAMMABLE

Keep away from fire or flame.

For external use only.

When using this product

• Do not use in or near eyes.

• In case of contact rinse eyes thoroughly with water.

Stop use and ask a doctor if

• irritation or rash appears and lasts.

Keep out of reach of Children. If swallowed get medical help or contact a Poison Control Center right away.

DOSAGE AND ADMINISTRATION

Directions • Apply product to hands and rub into skin until dry. Children under 6 yrs old should be supervised by an adult when using this product.

INACTIVE INGREDIENT

Inactive Ingredients: Essential Oil Blend, Vitis Vinifera (Grape) Seed Oil, Water (Aqua)

Other information

• Do not store above 104°F/40°C

• May discolor some fabrics.

KILLS 99.9% OF GERMS

original scent powered by natural essential oils.

Promotes proper hand hygiene and prevents the spread of hospital acquired infections

BACKED WITH GRAPESEED OIL to prevent dry cracked hands.

Distributed by: LaDiDah Essentials, LLC

PO BOX 2441 Gilbert, AZ 85288

LaDiDahEssentials.com